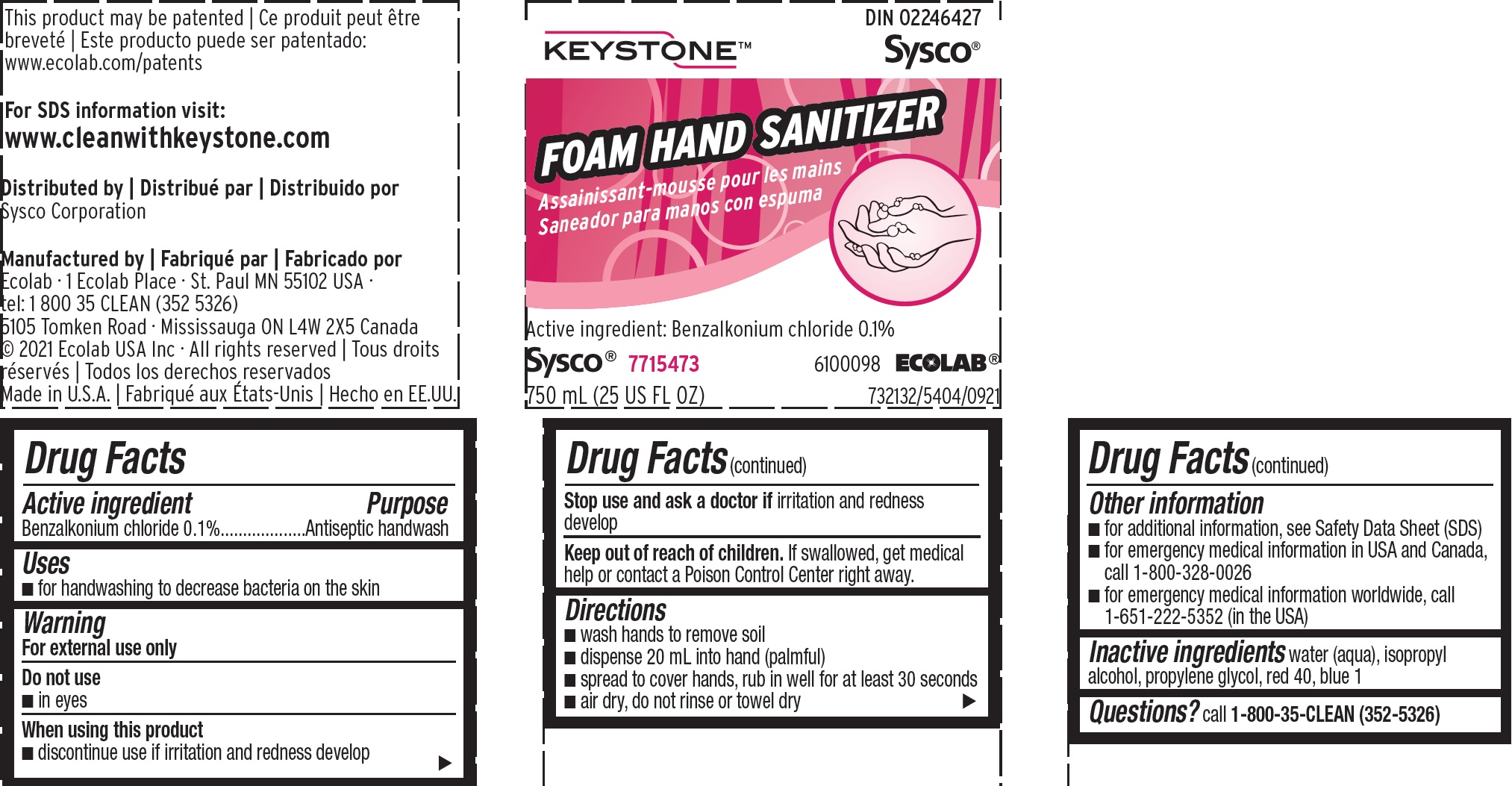 DRUG LABEL: Keystone 
NDC: 47593-359 | Form: SOLUTION
Manufacturer: Ecolab Inc.
Category: otc | Type: HUMAN OTC DRUG LABEL
Date: 20240319

ACTIVE INGREDIENTS: BENZALKONIUM CHLORIDE 0.1 mg/100 mL
INACTIVE INGREDIENTS: WATER; ISOPROPYL ALCOHOL; PROPYLENE GLYCOL; FD&C RED NO. 40; FD&C BLUE NO. 1

Drug Facts

Active ingredient

Benzalkonium chloride 0.1%

Purpose

Antiseptic handwash

Uses

- for handwashing to decrease bacteria on the skin

Warnings

For external use only

Do not use

- in eyes

When using this product

- discontinue use if irritation and redness develop

Stop use and ask a doctor if

irritation and redness develop

Keep out of reach of children. If swallowed, get medical help or contact a Poison Control Center right away.

Directions

- wash hands to remove soil
- dispense 20 mL into hand (palmful)
- spread to cover hands, rub in well for at least 30 seconds
- air dry, do not rinse or towel dry

Other information

- for additional information, see Safety Data Sheet (SDS)
- for emergency medical information in USA and Canada, call 1-800-328-0026
- for emergency medical information worldwide, call 1-651-222-5352 (in the USA)

INACTIVE INGREDIENT

Inactive ingredients water (aqua), isopropyl alcohol, propylene glycol, red 40, blue 1

Questions?

call 1-800-35-CLEAN (352-5326)

Primary Display Panel / Representative label

KEYSTONE SYSCO

FOAM HAND SANITIZER

Active Ingredient: Benzalkonium chloride 0.1%

Sysco 7715473 6100098 ECOLAB

750 ML (25 US FL OZ)

Distributed by

Sysco Corporation

Manufactured by:

Ecolab - 1 Ecolab Place - St. Paul MN 55102

tel: 1 800 35 CLEAN (352 5326)

(c) 2021 Ecolab USA Inc - All rights reserved

Made in U.S.A.